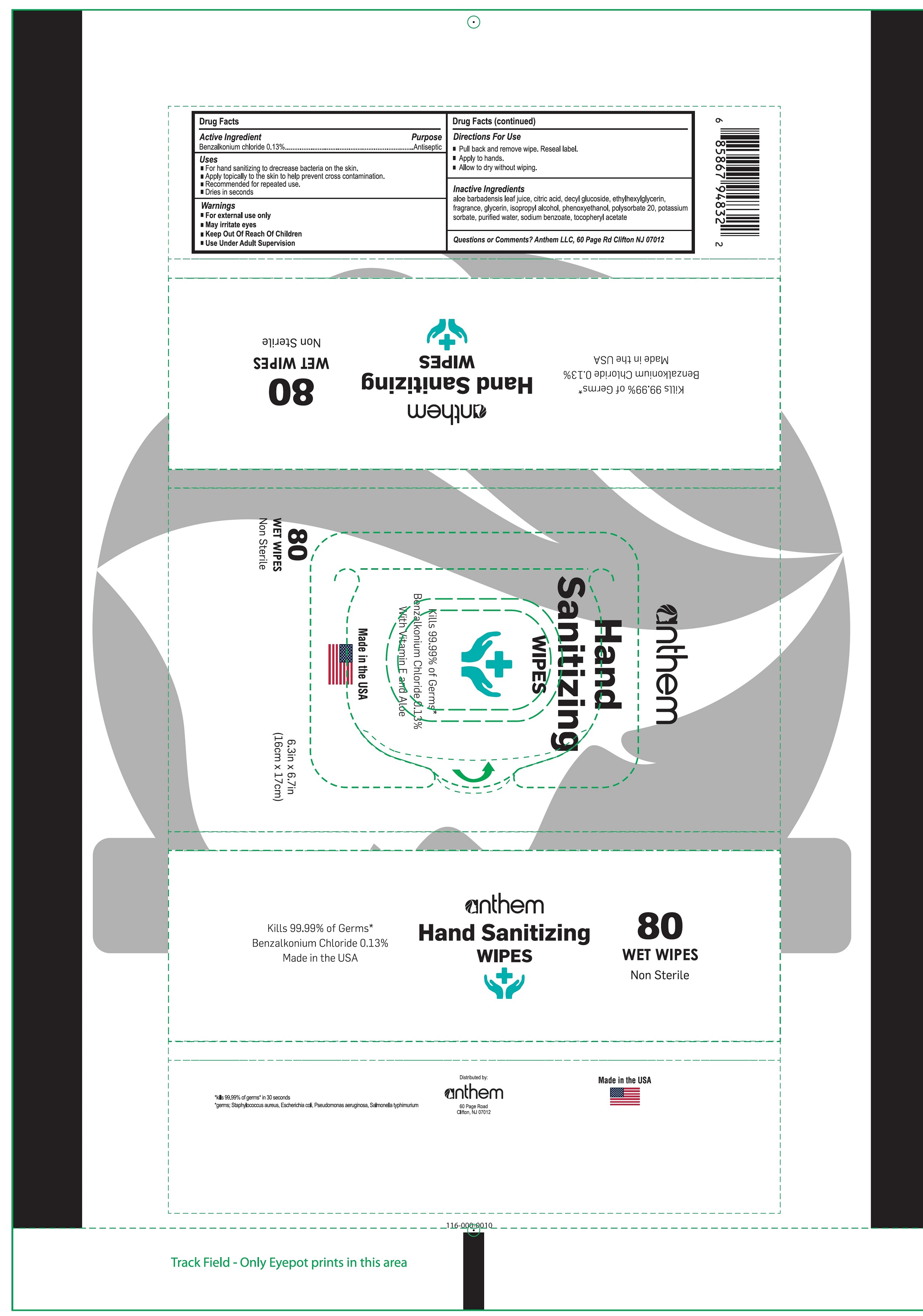 DRUG LABEL: Anthem Hand Sanitizing Wipes
NDC: 71505-004 | Form: CLOTH
Manufacturer: Disposable Hygiene LLC dba Anthem
Category: otc | Type: HUMAN OTC DRUG LABEL
Date: 20210212

ACTIVE INGREDIENTS: BENZALKONIUM CHLORIDE 1.3 mg/1 mL
INACTIVE INGREDIENTS: ALOE VERA LEAF; CITRIC ACID MONOHYDRATE; DECYL GLUCOSIDE; ETHYLHEXYLGLYCERIN; GLYCERIN; ISOPROPYL ALCOHOL; PHENOXYETHANOL; POLYSORBATE 20; POTASSIUM SORBATE; WATER; SODIUM BENZOATE; .ALPHA.-TOCOPHEROL ACETATE

Anthem Hand Sanitizing Wipes

Active Ingredient

Benzalkonium chloride 0.13%

Purpose

Antiseptic

Uses

- For hand sanitizing to decrease bacteria on the kin.
- Apply topically to the skin to help prevent cross contamination.
- Recommended for repeated use.
- Dries in seconds

Warnings

- For external use only
- May irritate eyes

Keep Out Of Reach Of Children

- Use Under Adult Supervision

Directions For Use

- Pull back and remove wipe. Reseal label.
- Apply to hands.
- Allow to dry without wiping.

Inactive Ingredients

Aloe barbadensis leaf juice, Citric acid, decyl glucoside, ethylhexylglycerin, fragrance, glycerin, isopropyl alcohol, phenoxyethanol, polysorbate 20, potassium sorbate, purified water, sodium benzoate, tocopheryl acetate

Questions or Comments?

Anthem LLC, 60 Page Rd Clifton NJ 07012